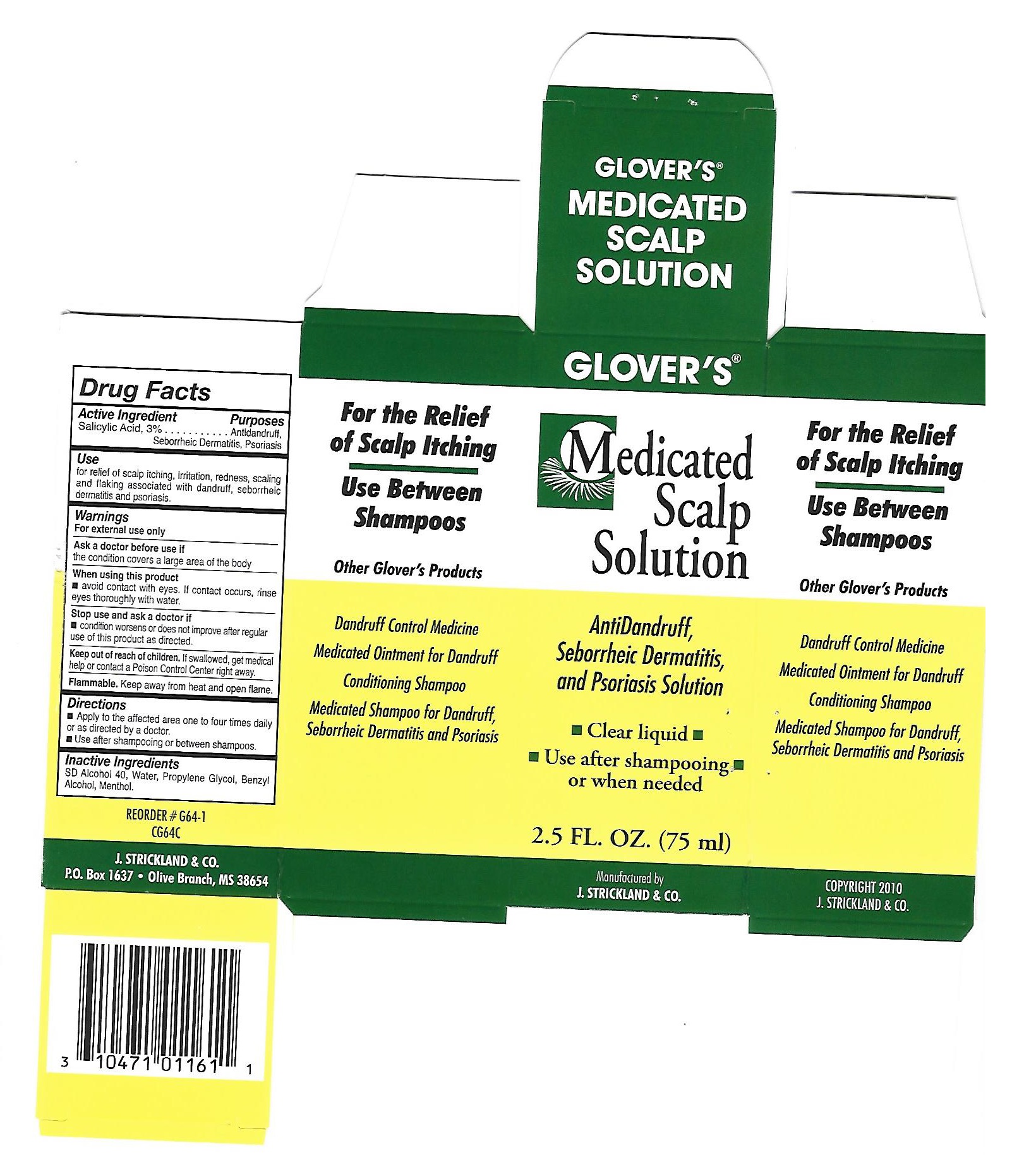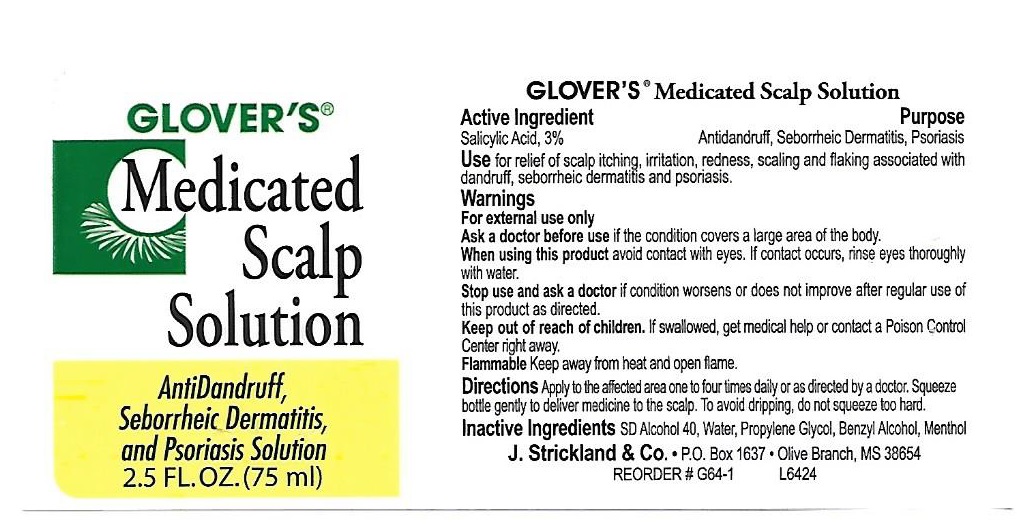 DRUG LABEL: Glovers Medicated Anti-Dandruff Scalp
NDC: 12022-011 | Form: SOLUTION
Manufacturer: J. Strickland & Co.
Category: otc | Type: HUMAN OTC DRUG LABEL
Date: 20231021

ACTIVE INGREDIENTS: SALICYLIC ACID 30 mg/1 mL
INACTIVE INGREDIENTS: WATER; PROPYLENE GLYCOL; BENZYL ALCOHOL; MENTHOL

Glover's Medicated Anti-Dandruff Scalp Solution

Active Ingredient

Salicylic Acid, 3%

Purposes

Antidandruff,

Seborrheic Dermatitis,

Psoriasis

Use

for relief of scalp itching, irritation, redness, scaling and flaking associated with dandruff, seborrheic dermatitis and psoriasis.

Warnings:

For External Use Only.

Ask a doctor before use if

the condition covers a large area of the body

When using this product

- avoid contact with eyes. If contact occurs, rinse eyes thoroughly with water.

Stop use and ask a doctor if

condition worsens or does not improve after regular use of this product as directed.

Keep out of reach of children

If swallowed, get medical help or call a poison control center right away.

Flammable

Keep away from heat and open flame.

Directions:

- Apply to the affected area one to four times daily or as directed by a doctor
- Use after shampooing or between shampoos.

Inactive Ingredients:

SD Alcohol 40, Water, Propylene Glycol, Benzyl Alcohol, Menthol.